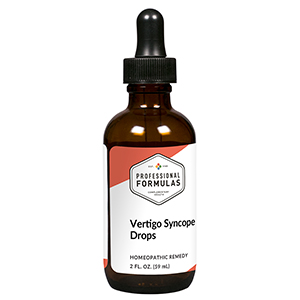 DRUG LABEL: Vertigo Syncope Drops
NDC: 63083-2115 | Form: LIQUID
Manufacturer: Professional Complementary Health Formulas
Category: homeopathic | Type: HUMAN OTC DRUG LABEL
Date: 20190815

ACTIVE INGREDIENTS: ARNICA MONTANA WHOLE 3 [hp_X]/59 mL; CENTELLA ASIATICA LEAF 3 [hp_X]/59 mL; PHOSPHORIC ACID 6 [hp_X]/59 mL; AMBERGRIS 12 [hp_X]/59 mL; SILVER NITRATE 12 [hp_X]/59 mL; ANAMIRTA COCCULUS FRUIT 12 [hp_X]/59 mL; CONIUM MACULATUM FLOWERING TOP 12 [hp_X]/59 mL; CANIS LUPUS FAMILIARIS MILK 12 [hp_X]/59 mL; THERIDION CURASSAVICUM 12 [hp_X]/59 mL
INACTIVE INGREDIENTS: ALCOHOL; WATER

C115

ACTIVE INGREDIENTS

Arnica montana 3X
Hydrocotyle asiatica 3X
Phosphoricum acidum 6X
Ambra grisea 12X
Argentum nitricum 12X
Cocculus indicus 12X
Conium maculatum 12X
Lac caninum 12X
Theridion 12X

QUESTIONS

Professional Formulas

PO Box 2034 Lake Oswego, OR 97035

INDICATIONS

For temporary relief of occasional dizziness or lightheadedness, loss of balance, nausea, or vomiting.*

PURPOSE

*Claims based on traditional homeopathic practice, not accepted medical evidence. Not FDA evaluated.

WARNINGS

Persistent symptoms may be a sign of a serious condition. If symptoms persist or are accompanied by a fever, persistent headache, stiff neck, or changes in vision or hearing, consult a doctor. Keep out of the reach of children. In case of overdose, get medical help or contact a poison control center right away. If pregnant or breastfeeding, ask a healthcare professional before use.

Keep out of the reach of children.

PREGNANCY OR BREAST FEEDING

If pregnant or breastfeeding, ask a healthcare professional before use.

DIRECTIONS

Place drops under tongue 30 minutes before/after meals. Adults and children 12 years and over: Take 10 drops up to 3 times per day for up to 6 weeks. For immediate onset of symptoms, take 10 to 15 drops every 15 minutes up to 3 hours. For less severe symptoms, take 10-15 drops hourly up to 8 hours. Consult a physician for use in children under 12 years of age.

OTHER INFORMATION

Tamper resistant. If seal is broken, do not use. After opening, close container tightly and store at room temperature away from heat.

INACTIVE INGREDIENTS

20% ethanol, purified water.

LABEL

Est 1985

Professional Formulas

Complementary Health

Vertigo Syncope Drops

Homeopathic Remedy

2 FL. OZ. (59 mL)